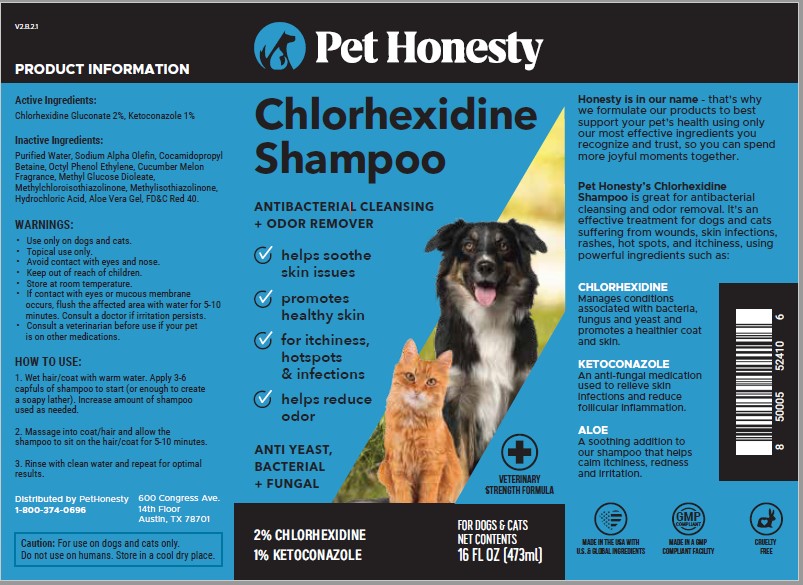 DRUG LABEL: CHLORHEXIDINE
NDC: 86177-101 | Form: SHAMPOO
Manufacturer: PetHonesty LLC
Category: animal | Type: OTC ANIMAL DRUG LABEL
Date: 20230321

ACTIVE INGREDIENTS: CHLORHEXIDINE GLUCONATE 2 g/100 mL; KETOCONAZOLE 1 g/100 mL
INACTIVE INGREDIENTS: WATER; SODIUM C14-16 OLEFIN SULFONATE; COCAMIDOPROPYL BETAINE; OCTOXYNOL 9; METHYL GLUCOSE DIOLEATE; METHYLCHLOROISOTHIAZOLINONE; METHYLISOTHIAZOLINONE; HYDROCHLORIC ACID; ALOE VERA LEAF; FD&C RED NO. 40

PetHonesty (as PLD) - Chlorhexidine Shampoo (86177-101)

ACTIVE INGREDIENTS:

CHLORHEXIDINE GLUCONATE 2%

KETOCONOZOLE 1%